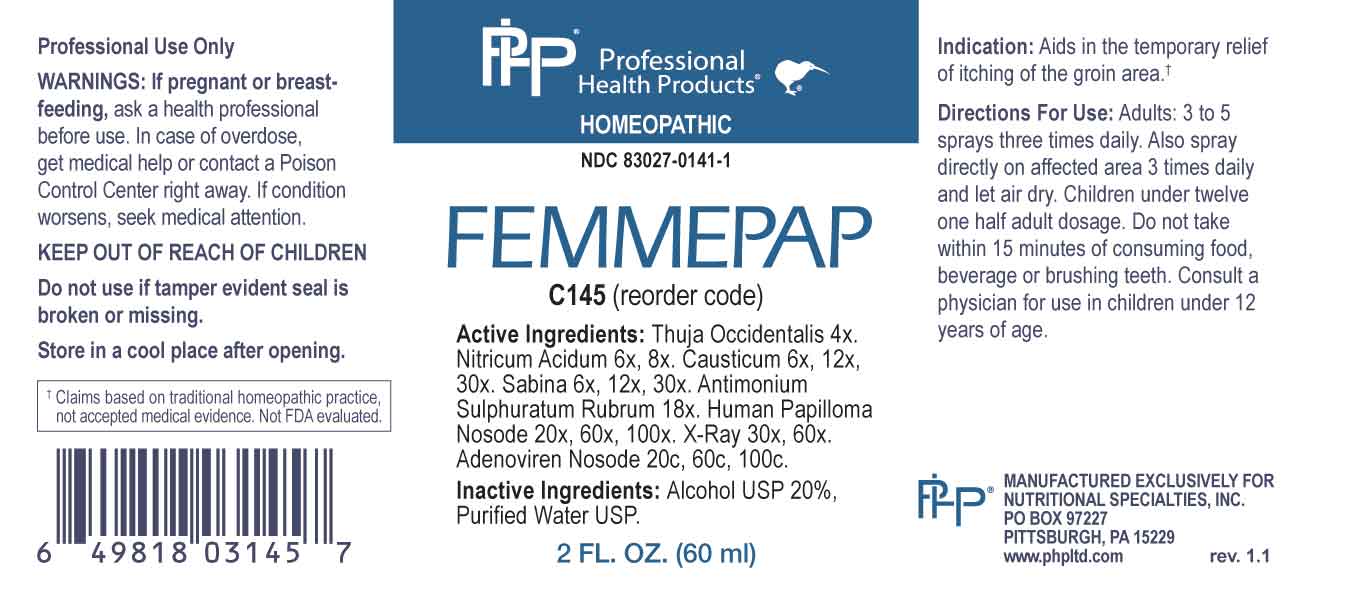 DRUG LABEL: Femmepap
NDC: 83027-0141 | Form: SPRAY
Manufacturer: Nutritional Specialties, Inc.
Category: homeopathic | Type: HUMAN OTC DRUG LABEL
Date: 20240725

ACTIVE INGREDIENTS: THUJA OCCIDENTALIS LEAFY TWIG 4 [hp_X]/1 mL; NITRIC ACID 6 [hp_X]/1 mL; CAUSTICUM 6 [hp_X]/1 mL; JUNIPERUS SABINA LEAFY TWIG 6 [hp_X]/1 mL; ANTIMONY OXIDE SULFIDE 18 [hp_X]/1 mL; HUMAN PAPILLOMAVIRUS 20 [hp_X]/1 mL; ALCOHOL, X-RAY EXPOSED (1000 RAD) 30 [hp_X]/1 mL; HUMAN ADENOVIRUS E SEROTYPE 4 STRAIN CL-68578 ANTIGEN 20 [hp_C]/1 mL
INACTIVE INGREDIENTS: WATER; ALCOHOL

DRUG FACTS:

ACTIVE INGREDIENTS:

Thuja Occidentalis 4X, Nitricum Acidum 6X, 8X, Causticum 6X, 12X, 30X, Sabina 6X, 12X, 30X, Antimonium Sulphuratum Rubrum 18X, Human Papilloma Nosode 20X, 60X, 100X, X-Ray 30X, 60X, Adenoviren Nosode 20C, 60C, 100C.

PURPOSE:

Aids in the temporary relief of itching of the groin area.†

†Claims based on traditional homeopathic practice, not accepted medical evidence. Not FDA evaluated.

WARNINGS:

Professional Use Only

If pregnant or breast-feeding, ask a health professional before use.

In case of overdose, get medical help or contact a Poison Control Center right away.

If condition worsens, seek medical attention.

KEEP OUT OF REACH OF CHILDREN

Do not use if tamper evident seal is broken or missing.

Store in a cool place after opening

KEEP OUT OF REACH OF CHILDREN:

In case of overdose, get medical help or contact a Poison Control Center right away.

DIRECTIONS:

Adults: 3 to 5 sprays three times daily. Also spray directly on affected area 3 times daily and let air dry. Children under twelve one half adult dosage. Do not take within 15 minutes of consuming food, beverage or brushing teeth. Consult a physician for use in children under 12 years of age.

INDICATIONS:

Aids in the temporary relief of itching of the groin area.†

†Claims based on traditional homeopathic practice, not accepted medical evidence. Not FDA evaluated.

INACTIVE INGREDIENTS:

Alcohol USP 20%, Purified Water USP.

QUESTIONS:

MANUFACTURED EXCLUSIVELY FOR

NUTRITIONAL SPECIALTIES, INC.

PO BOX 97227

PITTSBURG, PA 15229

www.phpltd.com

PACKAGE LABEL DISPLAY:

Professional

Health Products

HOMEOPATHIC

NDC 83027-0141-1

FEMMEPAP

2 FL. OZ (60 ml)